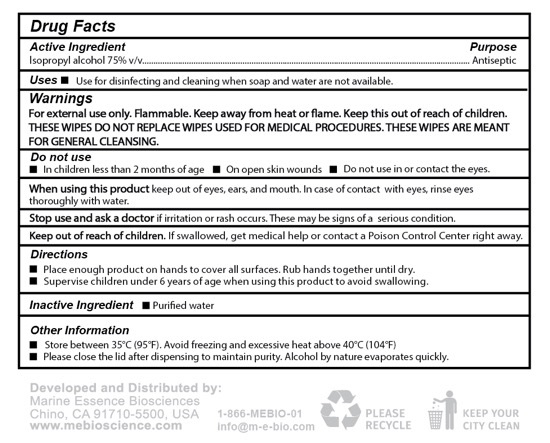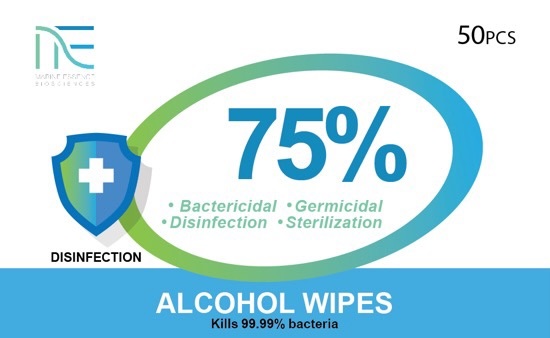 DRUG LABEL: 75% Alcohol Wipes
NDC: 73764-003 | Form: CLOTH
Manufacturer: Marine Essence Biosciences Corporation of USA
Category: otc | Type: HUMAN OTC DRUG LABEL
Date: 20200604

ACTIVE INGREDIENTS: ALCOHOL 0.75 U/1 U
INACTIVE INGREDIENTS: WATER

75% Alcohol Wipes

ACTIVE INGREDIENT

Alcohol 75% v/v

PURPOSE

Antiseptic

DOSAGE AND ADMINISTRATION

Cloth - A large piece of relatively flat, absorbent material that contains a drug. It is typically used for applying medication or for cleansing.

Topical - Administration outside of the body.

USE

Use for disinfecting and cleaning when soap and water are not available.

WARNINGS

For external use only.

Flammable.

Keep away from heat or flame.

Keep this out of reach of children.

THESE WIPES DO NOT REPLACE WIPES USED FOR MEDICAL PROCEDURES. THESE WIPES ARE MEANT FOR GENERAL CLEANSING.

DO NOT USE

In children less than 2 months of age.

On open skin wounds.

Do not use in or contact the eyes.

WHEN USING

When using this product keep out of eyes, ears, and mouth. In case of contact with eyes, rinse eyes thoroughly with water.

STOP USE

Stop use and ask a doctor if irritation or rash occurs. These may be signs of a serious condition.

KEEP OUT OF REACH OF CHILDREN

Keep out of reach of childred. If swallowed, get medical help or contact a Poison Control Center right away.

DIRECTIONS

Please enough product on hands to cover all surfaces. Rub hands together until dry.

Supervise children under 6 years of age when using this product to avoid swallowing.

INACTIVE INGREDIENT

Purified water

OTHER INFORMATION

Store below 35°C (95°F). Avoid freezing and excessing heat above 40°C (104°F).

Please close the lid after dispensing to maintain purity. Alcohol by nature evaporates quickly.